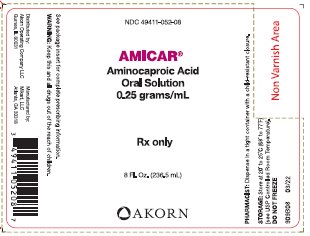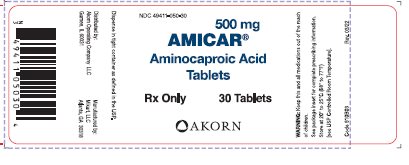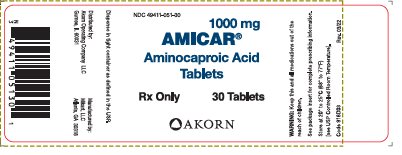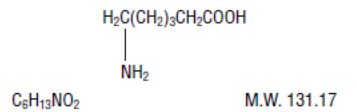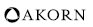 DRUG LABEL: AMICAR
NDC: 49411-052 | Form: SOLUTION
Manufacturer: Akorn Operating Company LLC
Category: prescription | Type: HUMAN PRESCRIPTION DRUG LABEL
Date: 20220628

ACTIVE INGREDIENTS: AMINOCAPROIC ACID 0.25 g/1 mL
INACTIVE INGREDIENTS: METHYLPARABEN; PROPYLPARABEN; EDETATE DISODIUM; SACCHARIN SODIUM; SORBITOL; ANHYDROUS CITRIC ACID; RASPBERRY

AMICAR® (aminocaproic acid)
Oral Solution and Tablets

Rx only

DESCRIPTION

AMICAR (aminocaproic acid) is 6-aminohexanoic acid, which acts as an inhibitor of fibrinolysis.

Its chemical structure is:

AMICAR is soluble in water, acid, and alkaline solutions; it is sparingly soluble in methanol and practically insoluble in chloroform.

AMICAR (aminocaproic acid) Oral Solution for oral administration, contains 0.25 g/mL of aminocaproic acid with methylparaben 0.20%, propylparaben 0.05%, edetate disodium 0.30% as preservatives and the following inactive ingredients: sodium saccharin, sorbitol solution, citric acid anhydrous, natural and artificial raspberry flavor and an artificial bitterness modifier.

Each AMICAR (aminocaproic acid) Tablet, for oral administration contains 500 mg or 1000 mg of aminocaproic acid and the following inactive ingredients: povidone, crospovidone, stearic acid, and magnesium stearate.

CLINICAL PHARMACOLOGY

The fibrinolysis-inhibitory effects of AMICAR appear to be exerted principally via inhibition of plasminogen activators and to a lesser degree through antiplasmin activity.

In adults, oral absorption appears to be a zero-order process with an absorption rate of 5.2 g/hr. The mean lag time in absorption is 10 minutes. After a single oral dose of 5 g, absorption was complete (F=1). Mean ± SD peak plasma concentrations (164 ± 28 mcg/mL) were reached within 1.2 ± 0.45 hours.

After oral administration, the apparent volume of distribution was estimated to be 23.1 ± 6.6 L (mean ± SD). Correspondingly, the volume of distribution after intravenous administration has been reported to be 30.0 ± 8.2 L. After prolonged administration, AMICAR has been found to distribute throughout extravascular and intravascular compartments of the body, penetrating human red blood cells as well as other tissue cells.

Renal excretion is the primary route of elimination. Sixty-five percent of the dose is recovered in the urine as unchanged drug and 11% of the dose appears as the metabolite adipic acid. Renal clearance (116 mL/min) approximates endogenous creatinine clearance. The total body clearance is 169 mL/min. The terminal elimination half-life for AMICAR is approximately 2 hours.

INDICATIONS AND USAGE

AMICAR is useful in enhancing hemostasis when fibrinolysis contributes to bleeding. In life-threatening situations, transfusion of appropriate blood products and other emergency measures may be required.

Fibrinolytic bleeding may frequently be associated with surgical complications following heart surgery (with or without cardiac bypass procedures) and portacaval shunt; hematological disorders such as amegakaryocytic thrombocytopenia (accompanying aplastic anemia); acute and life-threatening abruptio placentae; hepatic cirrhosis; and neoplastic disease such as carcinoma of the prostate, lung, stomach, and cervix.

Urinary fibrinolysis, usually a normal physiological phenomenon, may contribute to excessive urinary tract fibrinolytic bleeding associated with surgical hematuria (following prostatectomy and nephrectomy) or nonsurgical hematuria (accompanying polycystic or neoplastic diseases of the genitourinary system). (See WARNINGS.)

CONTRAINDICATIONS

AMICAR should not be used when there is evidence of an active intravascular clotting process.

When there is uncertainty as to whether the cause of bleeding is primary fibrinolysis or disseminated intravascular coagulation (DIC), this distinction must be made before administering AMICAR.

The following tests can be applied to differentiate the two conditions:

Platelet count is usually decreased in DIC but normal in primary fibrinolysis.

Protamine paracoagulation test is positive in DIC; a precipitate forms when protamine sulfate is dropped into citrated plasma. The test is negative in the presence of primary fibrinolysis.

The euglobulin clot lysis test is abnormal in primary fibrinolysis but normal in DIC.

AMICAR must not be used in the presence of DIC without concomitant heparin.

WARNINGS

In patients with upper urinary tract bleeding, AMICAR administration has been known to cause intrarenal obstruction in the form of glomerular capillary thrombosis or clots in the renal pelvis and ureters. For this reason, AMICAR should not be used in hematuria of upper urinary tract origin, unless the possible benefits outweigh the risk.

Subendocardial hemorrhages have been observed in dogs given intravenous infusions of 0.2 times the maximum human therapeutic dose of AMICAR and in monkeys given 8 times the maximum human therapeutic dose of AMICAR.

Fatty degeneration of the myocardium has been reported in dogs given intravenous doses of AMICAR at 0.8 to 3.3 times the maximum human therapeutic dose and in monkeys given intravenous doses of AMICAR at 6 times the maximum human therapeutic dose.

Rarely, skeletal muscle weakness with necrosis of muscle fibers has been reported following prolonged administration. Clinical presentation may range from mild myalgias with weakness and fatigue to a severe proximal myopathy with rhabdomyolysis, myoglobinuria, and acute renal failure. Muscle enzymes, especially creatine phosphokinase (CPK) are elevated. CPK levels should be monitored in patients on long-term therapy. AMICAR administration should be stopped if a rise in CPK is noted. Resolution follows discontinuation of AMICAR; however, the syndrome may recur if AMICAR is restarted.

The possibility of cardiac muscle damage should also be considered when skeletal myopathy occurs. One case of cardiac and hepatic lesions observed in man has been reported. The patient received 2 g of aminocaproic acid every 6 hours for a total dose of 26 g. Death was due to continued cerebrovascular hemorrhage. Necrotic changes in the heart and liver were noted at autopsy.

PRECAUTIONS

General

AMICAR inhibits both the action of plasminogen activators and to a lesser degree, plasmin activity. The drug should NOT be administered without a definite diagnosis and/or laboratory finding indicative of hyperfibrinolysis (hyperplasminemia).^1 Inhibition of fibrinolysis by aminocaproic acid may theoretically result in clotting or thrombosis. However, there is no definite evidence that administration of aminocaproic acid has been responsible for the few reported cases of intravascular clotting which followed this treatment. Rather, it appears that such intravascular clotting was most likely due to the patient's preexisting clinical condition, e.g., the presence of DIC. It has been postulated that extravascular clots formed in vivo may not undergo spontaneous lysis as do normal clots.

Reports have appeared in the literature of an increased incidence of certain neurological deficits such as hydrocephalus, cerebral ischemia, or cerebral vasospasm associated with the use of antifibrinolytic agents in the treatment of subarachnoid hemorrhage (SAH). All of these events have also been described as part of the natural course of SAH, or as a consequence of diagnostic procedures such as angiography. Drug relatedness remains unclear.

Aminocaproic acid should not be administered with Factor IX Complex concentrates or Anti-Inhibitor Coagulant concentrates, as the risk of thrombosis may be increased.

Laboratory Tests

The use of AMICAR should be accompanied by tests designed to determine the amount of fibrinolysis present. There are presently available: (a) general tests such as those for the determination of the lysis of a clot of blood or plasma; and (b) more specific tests for the study of various phases of the fibrinolytic mechanisms. These latter tests include both semiquantitative and quantitative techniques for the determination of profibrinolysin, fibrinolysin, and antifibrinolysin.

Drug Laboratory Test Interactions

Prolongation of the template bleeding time has been reported during continuous intravenous infusion of AMICAR at dosages exceeding 24 g/day. Platelet function studies in these patients have not demonstrated any significant platelet dysfunction. However, in vitro studies have shown that at high concentrations (7.4 mMol/L or 0.97 mg/mL and greater) aminocaproic acid inhibits ADP and collagen-induced platelet aggregation, the release of ATP and serotonin, and the binding of fibrinogen to the platelets in a concentration-response manner. Following a 10 g bolus of AMICAR, transient peak plasma concentrations of 4.6 mMol/L or 0.60 mg/mL have been obtained. The concentration of AMICAR necessary to maintain inhibition of fibrinolysis is 0.99 mMol/L or 0.13 mg/mL. Administration of a 5 g bolus followed by 1 to 1.25 g/hr should achieve and sustain plasma levels of 0.13 mg/mL. Thus, concentrations which have been obtained in vivo clinically in patients with normal renal function are considerably lower than the in vitro concentrations found to induce abnormalities in platelet function tests. However, higher plasma concentrations of AMICAR may occur in patients with severe renal failure.

Carcinogenesis, Mutagenesis, Impairment of Fertility

Long-term studies in animals to evaluate the carcinogenic potential of AMICAR and studies to evaluate its mutagenic potential have not been conducted. Dietary administration of an equivalent of the maximum human therapeutic dose of AMICAR to rats of both sexes impaired fertility as evidenced by decreased implantations, litter sizes and number of pups born.

Pregnancy

Pregnancy Category C. Animal reproduction studies have not been conducted with AMICAR. It is also not known whether AMICAR can cause fetal harm when administered to a pregnant woman or can affect reproduction capacity. AMICAR should be given to a pregnant woman only if clearly needed.

Nursing Mothers

It is not known whether this drug is excreted in human milk. Because many drugs are excreted in human milk, caution should be exercised when AMICAR is administered to a nursing woman.

Pediatric Use

Safety and effectiveness in pediatric patients have not been established.

ADVERSE REACTIONS

AMICAR is generally well tolerated. The following adverse experiences have been reported:

General: Edema, headache, malaise.

Hypersensitivity Reactions: Allergic and anaphylactoid reactions, anaphylaxis.

Cardiovascular: Bradycardia, hypotension, peripheral ischemia, thrombosis.

Gastrointestinal: Abdominal pain, diarrhea, nausea, vomiting.

Hematologic: Agranulocytosis, coagulation disorder, leukopenia, thrombocytopenia.

Musculoskeletal: CPK increased, muscle weakness, myalgia, myopathy (see WARNINGS), myositis, rhabdomyolysis.

Neurologic: Confusion, convulsions, delirium, dizziness, hallucinations, intracranial hypertension, stroke, syncope.

Respiratory: Dyspnea, nasal congestion, pulmonary embolism.

Skin: Pruritis, rash.

Special Senses: Tinnitus, vision decreased, watery eyes.

Urogenital: BUN increased, renal failure. There have been some reports of dry ejaculation during the period of AMICAR treatment. These have been reported to date only in hemophilia patients who received the drug after undergoing dental surgical procedures. However, this symptom resolved in all patients within 24 to 48 hours of completion of therapy.

OVERDOSAGE

A few cases of acute overdosage with AMICAR administered intravenously have been reported. The effects have ranged from no reaction to transient hypotension to severe acute renal failure leading to death. One patient with a history of brain tumor and seizures experienced seizures after receiving an 8 gram bolus injection of AMICAR. The single dose of AMICAR causing symptoms of overdosage or considered to be life-threatening is unknown. Patients have tolerated doses as high as 100 grams while acute renal failure has been reported following a dose of 12 grams.

The intravenous and oral LD50 of AMICAR were 3.0 and 12.0 g/kg, respectively, in the mouse and 3.2 and 16.4 g/kg, respectively, in the rat. An intravenous infusion dose of 2.3 g/kg was lethal in the dog. On intravenous administration, tonic-clonic convulsions were observed in dogs and mice.

No treatment for overdosage is known, although evidence exists that AMICAR is removed by hemodialysis and may be removed by peritoneal dialysis. Pharmacokinetic studies have shown that total body clearance of AMICAR is markedly decreased in patients with severe renal failure.

DOSAGE AND ADMINISTRATION

An identical dosage regimen may be followed by administering AMICAR Tablets or AMICAR Oral Solution as follows:

For the treatment of acute bleeding syndromes due to elevated fibrinolytic activity, it is suggested that 5 AMICAR 1000 mg Tablets or 10 AMICAR 500 mg Tablets (5 g) or 20 milliliter of AMICAR Oral Solution (5 g) be administered during the first hour of treatment, followed by a continuing rate of 1 AMICAR 1000 mg Tablet or 2 AMICAR 500 mg Tablets (1 g) or 5 milliliter of AMICAR Oral Solution (1.25 g) per hour. This method of treatment would ordinarily be continued for about 8 hours or until the bleeding situation has been controlled.

HOW SUPPLIED

AMICAR®
(aminocaproic acid)

AMICAR Oral Solution, 0.25 g/mL

Each mL of raspberry-flavored oral solution contains 0.25 g/mL of aminocaproic acid.

8 Fl. Oz. (236.5 mL) Bottle – NDC 49411-052-08

Store at 20°-25°C (68°-77°F)[see USP Controlled Room Temperature];Dispense in Tight Containers; Do Not Freeze.

AMICAR 500 mg Tablets

Each round, white tablet, engraved with XP on one side and scored on the other with A to the left of the score and 10 on the right, contains 500 mg of aminocaproic acid.

Bottle of 30 – NDC 49411-050-30

Store at 20°-25°C (68°-77°F)[see USP Controlled Room Temperature];Dispense in Tight Containers; Do Not Freeze.

AMICAR 1000 mg Tablets

Each oblong, white tablet, engraved with XP on one side and scored on the other with A to the left of the score and 20 on the right, contains 1000 mg of aminocaproic acid.

Bottle of 30 – NDC 49411-051-30

Store at 20°-25°C (68°-77°F)[see USP Controlled Room Temperature];Dispense in Tight Containers; Do Not Freeze.

REFERENCE

^1 Stefanini M, Dameshek W: The Hemorrhagic Disorders, Ed. 2, New York, Grune and Stratton; 1962:510-514.

Distributed by:

Akorn Operating Company LLC

Gurnee, IL 60031

Manufactured by:

Mikart, LLC

Atlanta, GA 30318

Code 909B00
Rev. 03/22

PACKAGE/LABEL PRINCIPAL DISPLAY PANEL

Bottle Label – 8 Fl. Oz. (236.5 mL)
NDC 49411-052-08
AMICAR®
Aminocaproic Acid
Oral Solution
0.25 grams/mL
Rx only
8 Fl. Oz. (236.5 mL)

PACKAGE/LABEL PRINCIPAL DISPLAY PANEL

Bottle Label – 500 mg
NDC 49411-050-30
500 mg
AMICAR®
Aminocaproic Acid
Tablets
Rx Only
30 Tablets

PACKAGE/LABEL PRINCIPAL DISPLAY PANEL

Bottle Label – 1000 mg
NDC 49411-051-30
1000 mg
AMICAR®
Aminocaproic Acid
Tablets
Rx Only
30 Tablets